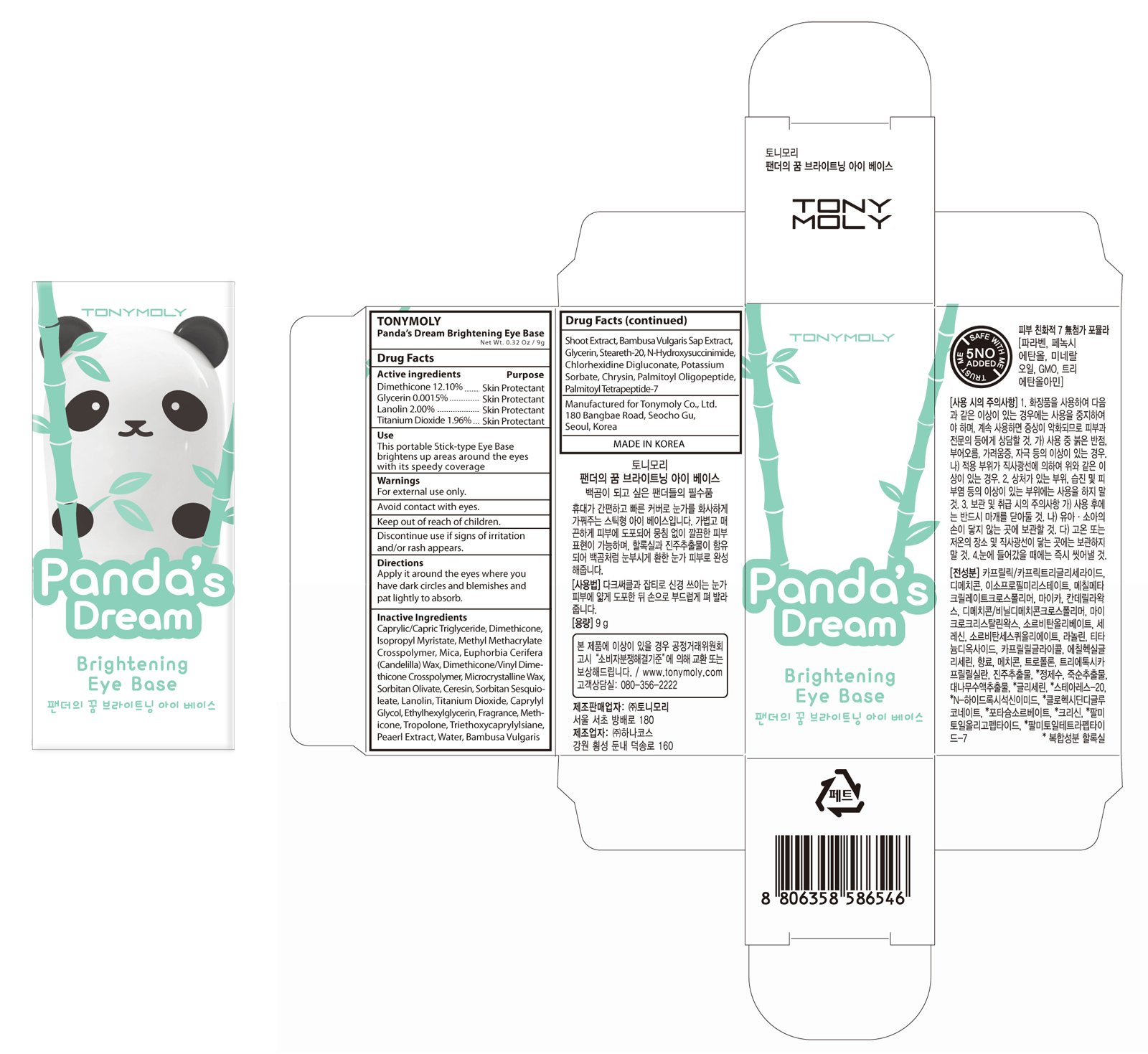 DRUG LABEL: TONYMOLY Pandas Dream Brightening Eye Base
NDC: 59078-150 | Form: CREAM
Manufacturer: Tonymoly Co., Ltd.
Category: otc | Type: HUMAN OTC DRUG LABEL
Date: 20160210

ACTIVE INGREDIENTS: TITANIUM DIOXIDE 0.1764 g/9 g; LANOLIN 0.18 g/9 g; GLYCERIN 0.000135 g/9 g; DIMETHICONE 1.089 g/9 g
INACTIVE INGREDIENTS: SORBITAN OLIVATE; CANDELILLA WAX; TRIETHOXYCAPRYLYLSILANE; CHRYSIN; CERESIN; WATER; SORBITAN SESQUIOLEATE; BUTYLENE GLYCOL; MEDIUM-CHAIN TRIGLYCERIDES; ISOPROPYL MYRISTATE; CAPRYLYL GLYCOL; ETHYLHEXYLGLYCERIN; CYCLOMETHICONE 5; ALCOHOL; TROPOLONE; MICA; PEARL (HYRIOPSIS CUMINGII); BAMBUSA VULGARIS SAP; STEARETH-20; N-HYDROXYSUCCINIMIDE; CHLORHEXIDINE GLUCONATE; POTASSIUM SORBATE; PALMITOYL TETRAPEPTIDE-7

Active Ingredients

Dimethicone 12.10%, Glycerin 0.0015%, Lanolin 2.00%, Titanium Dioxide 1.96%

Purpose

Skin Protectant

Use

This portable Stick-type Eye Base brightens up areas around the eyes with its speedy coverage.

Caution

For external use only. Avoid contact with eyes. Keep out of reach of children. Discontinue use if signs of irritation and/or rash appear.

Keep out of reach of children

Directions

Apply it around the eyes where you have dark circles and blemishes and pat lightly to absorb.

Inactive Ingredients

Caprylic/Capric Triglyceride, Isopropyl Myristate, Methyl Methacrylate Crosspolymer, Mica, Euphorbia Cerifera (Candelilla) Wax, Dimethicone/Vinyl Dimethicone, Crosspolymer, Microcrystalline Wax, Sorbitan Olivate, Ceresin, Sorbitan Sesquioleate, Caprylyl Glycol, Ethylhexylglycerin, Fragrance, Methicone, Tropolone, Triethoxycaprylylsilane, Pearl Extract, Water, Bambusa Vulgaris Shoot Extract, Bambusa Vulgaris Sap Extract, Steareth-20, N-Hydroxysuccinimide, Chlorhexidine Digluconate, Potassium Sorbate, Chrysin, Palmitoyl Oligopeptide, Palmitoyl Tetrapeptide-7